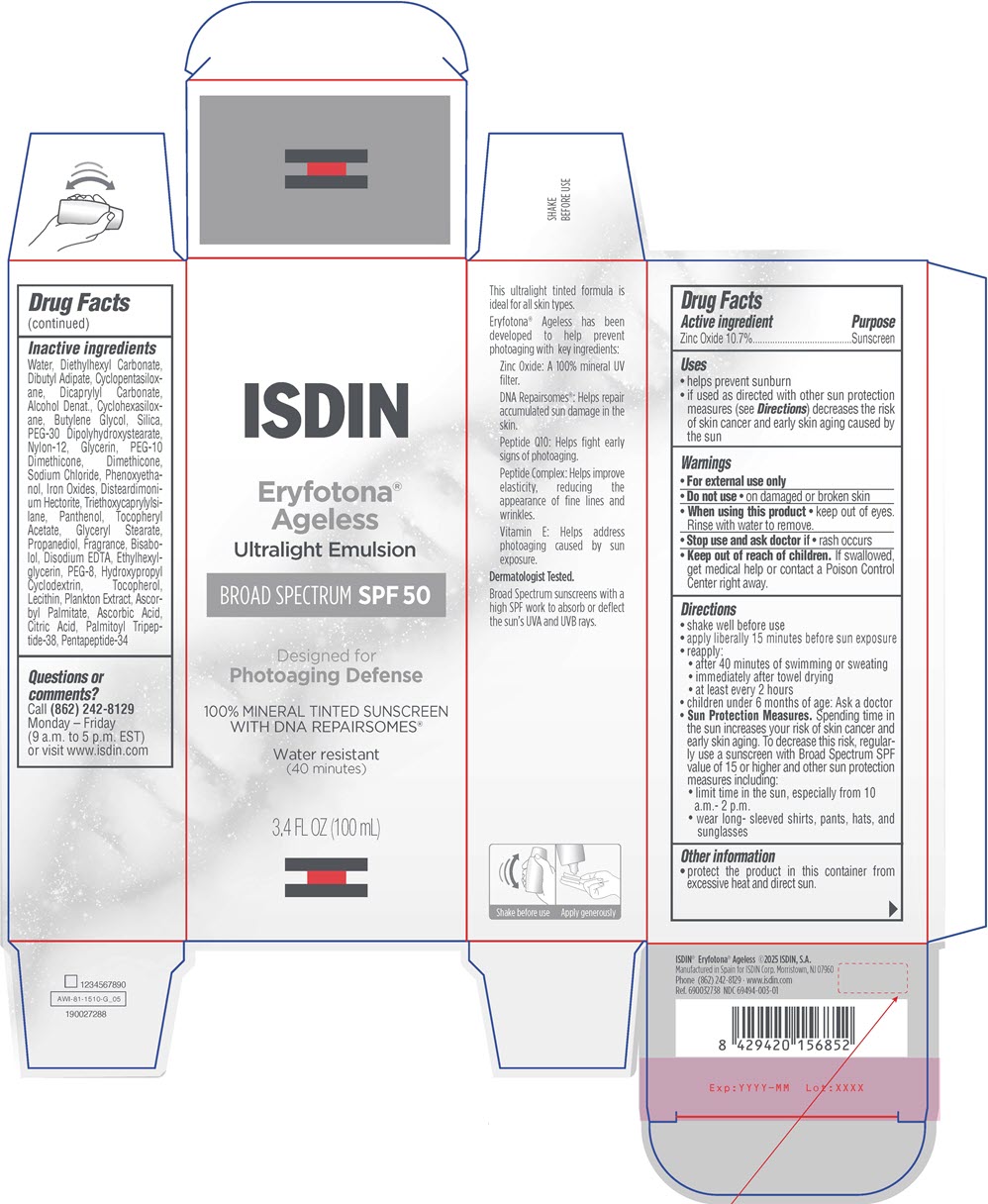 DRUG LABEL: Eryfotona Ageless
NDC: 69494-003 | Form: LOTION
Manufacturer: ISDIN Corp.
Category: otc | Type: HUMAN OTC DRUG LABEL
Date: 20260223

ACTIVE INGREDIENTS: Zinc Oxide 107 mg/1 mL
INACTIVE INGREDIENTS: SOYBEAN LECITHIN; Disteardimonium Hectorite; CITRIC ACID MONOHYDRATE; Dibutyl Adipate; Butylene Glycol; Sodium Chloride; Panthenol; Water; Nylon-12; PEG-10 DIMETHICONE (600 CST); SILICON DIOXIDE; Glycerin; Dimethicone; LEVOMENOL; .ALPHA.-Tocopherol Acetate; Ethylhexylglycerin; EDETATE DISODIUM ANHYDROUS; Propanediol; GLYCERYL MONOSTEARATE; Tocopherol; Ascorbyl Palmitate; Alcohol; Denatonium Benzoate; Pentapeptide-34; CYCLOMETHICONE 5; Diethylhexyl Carbonate; Ascorbic Acid; Ferric Oxide Red; FERROSOFERRIC OXIDE; Ferric Oxide Yellow; CYCLOMETHICONE 6; Dicaprylyl Carbonate; Phenoxyethanol; PEG-30 DIPOLYHYDROXYSTEARATE (4000 MW); Triethoxycaprylylsilane; PALMITOYL TRIPEPTIDE-38; POLYETHYLENE GLYCOL 400; HYDROXYPROPYL BETADEX; Pentapeptide-34 Trifluoroacetate; Sodium Benzoate

Eryfotona® Ageless

Drug Facts

Active ingredient

Zinc Oxide 10.7%

Purpose

Sunscreen

Uses

- Helps prevent sunburn.
- If used as directed with other sun protection measures (see Directions) decreases the risk of skin cancer and early skin aging caused by the sun.

Warning

- For external use only.

- Do not use on damaged or broken skin.

- When using this product keep out of eyes. Rinse with water to remove.

- Stop use and ask doctor if rash occurs.

- Keep out of reach of children. If product is swallowed, get medical help or contact a Poison Control Center right away.

Directions

- Apply liberally 15 minutes before sun exposure.
- During sun exposure, reapply:
  - after 40 minutes of swimming or sweating.
  - immediately after towel drying.
  - at least every 2 hours.
- Sun Protection Measures: Spending time in the sun increases the risk of skin cancer and early skin aging. To decrease this risk, regularly use a sunscreen with broad spectrum SPF value of 15 or higher and other sun protection measures including:
  - limit time in the sun, especially from 10 a.m.- 2 p.m.
  - wear long- sleeve shirts, pants, hats and sunglasses.
- Children under 6 months: ask a doctor.

Other information

- Protect the product in this container from excessive heat and direct sun.

Inactive ingredients

Water, Diethylhexyl Carbonate, Dibutyl Adipate, Cyclopentasiloxane, Dicaprylyl Carbonate, Alcohol Denat., Cyclohexasiloxane, Butylene Glycol, Silica, PEG-30 Dipolyhydroxystearate, Nylon-12, Glycerin, PEG-10 Dimethicone, Dimethicone, Sodium Chloride, Phenoxyethanol, Iron Oxides, Disteardimonium Hectorite, Triethoxycaprylylsilane, Panthenol, Tocopheryl Acetate, Glyceryl Stearate, Propanediol, Fragrance, Bisabolol, Disodium EDTA, Ethylhexylglycerin, PEG-8, Hydroxypropyl Cyclodextrin, Tocopherol, Lecithin, Plankton Extract, Ascorbyl Palmitate, Sodium Benzoate, Ascorbic Acid, Citric Acid, Palmitoyl Tripeptide-38, Pentapeptide-34 Trifluoroacetate.

Questions or comments?

Call (862) 242-8129
Monday – Friday
(9 a.m. to 5 p.m. EST)
or visit www.isdin.com

PRINCIPAL DISPLAY PANEL - 100 mL Bottle Carton

ISDIN

Eryfotona®
Ageless
Ultralight Emulsion

BROAD SPECTRUM SPF 50

Designed for
Photoaging Defense

100% MINERAL TINTED SUNSCREEN
WITH DNA REPAIRSOMES®

Water resistant
(40 minutes)

3.4 FL OZ (100 mL)